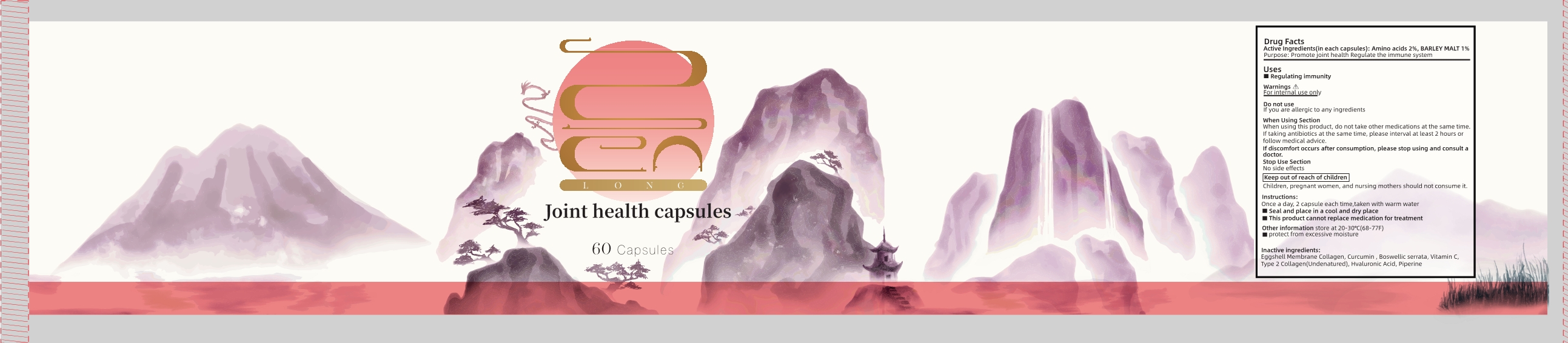 DRUG LABEL: Joint health
NDC: 83739-001 | Form: CAPSULE
Manufacturer: XIAN CHIANG COMPANY LIMITED
Category: otc | Type: HUMAN OTC DRUG LABEL
Date: 20250214

ACTIVE INGREDIENTS: AMINO ACIDS 2 g/100 1; BARLEY MALT 1 g/100 1
INACTIVE INGREDIENTS: ASCORBIC ACID; PIPERINE; HYALURONIC ACID; CURCUMIN; INDIAN FRANKINCENSE; PENICILLOYL POLYLYSINE; HUMAN TYPE V COLLAGEN

83739-001

ACTIVE INGREDIENT

Amino acids 2%, BARLEY MALT 1%

Purpose

Promote joint health Regulate the immune system

Uses

Regulating immunity

Warnings

For internal use only

Do not use

If you are allergic to any ingredients

Stop Use Section

No side effects

When Using Section

When using this product , do not take other medications at the same time, If taking antibiotics at the same time , please interval at least 2 hours or follow medical advice

If discomfort occurs after consumption , please stop using and consult a doctor

Keep out of reach of children

Children , pregnant women , and nursing mothers should not consume it .

Instructions

Once a day , 2 capsule each time , taken with warm water

Seal and place in a cool and dry place

This product cannot replace medication for treatment

Other information

Other information store at 20-30°C (68-77F)

protect from excessive moisture

Inactive ingredients

Eggshell Membrane Collagen , Curcumin , Boswellic serrata , Vitamin C, Type 2 Collagen (Undenatured) , Hvaluronic Acid , Piperine